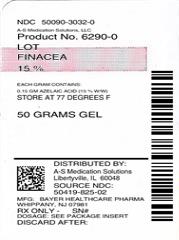 DRUG LABEL: Finacea
NDC: 50090-3032 | Form: GEL
Manufacturer: A-S Medication Solutions
Category: prescription | Type: HUMAN PRESCRIPTION DRUG LABEL
Date: 20200118

ACTIVE INGREDIENTS: AZELAIC ACID 0.15 g/1 g
INACTIVE INGREDIENTS: BENZOIC ACID; EDETATE DISODIUM; 1,2-DIARACHIDOYL-SN-GLYCERO-3-PHOSPHOCHOLINE; MEDIUM-CHAIN TRIGLYCERIDES; POLYACRYLIC ACID (250000 MW); POLYSORBATE 80; PROPYLENE GLYCOL; SODIUM HYDROXIDE; WATER

HIGHLIGHTS OF PRESCRIBING INFORMATION

These highlights do not include all the information needed to use FINACEA® Gel safely and effectively. See full prescribing information for FINACEA Gel.
FINACEA® (azelaic acid) Gel, 15% for topical use
Initial U.S. Approval: 1995

RECENT MAJOR CHANGES

Warnings and Precautions:

Worsening Exacerbation of Asthma (5.4) 8/2016

1 INDICATIONS AND USAGE

FINACEA® (azelaic acid) Gel, 15% is indicated for topical treatment of the inflammatory papules and pustules of mild to moderate rosacea. Efficacy for treatment of erythema in rosacea in the absence of papules and pustules has not been evaluated. (1)

2 DOSAGE AND ADMINISTRATION

- Apply a thin layer of FINACEA Gel twice daily to affected area(s). (2)
- Use only very mild soaps or soapless cleansing lotion before applying FINACEA Gel. (2)
- Cosmetics may be applied after the application of FINACEA Gel has dried. (2)
- Avoid spicy foods, thermally hot foods and drinks, alcoholic beverages. (2)
- Not for oral, ophthalmic or intravaginal use. (2)

3 DOSAGE FORMS AND STRENGTHS

Gel, 15% (3)

4 CONTRAINDICATIONS

None. (4)

5 WARNINGS AND PRECAUTIONS

- Hypersensitivity: In case of known hypersensitivity to any component of the gel, avoid the use of FINACEA Gel. If hypersensitivity develops during treatment, discontinue FINACEA Gel and institute appropriate therapy. (5.1)
- Skin Reactions: Skin irritation (i.e. pruritus, burning or stinging) may occur, usually during the first few weeks of treatment with FINACEAGel. If sensitivity or severe irritation develops and persists, discontinue treatment and institute appropriate therapy. (5.2)
- Hypopigmentation: Isolated cases of hypopigmentation occurred after azelaic acid use. Monitor patients with dark complexion for early signs of hypopigmentation (5.2)
- Eye and Mucous Membrane Irritation: FINACEAGel has been reported to cause irritation of the eyes. Therefore, avoid contact with the eyes and mucous membranes. (5.3)
- Exacerbation of Asthma: Consult a physician if asthma is exacerbated with FINACEA Gel use. (5.4)

6 ADVERSE REACTIONS

The most common adverse reactions are burning/stinging/tingling (29%), pruritus (11%), scaling/dry skin/xerosis (8%) and erythema/irritation (4%). (6)

To report SUSPECTED ADVERSE REACTIONS, contact Bayer HealthCare at 1-866-463-3634 or FDA at 1-800-FDA-1088 or www.fda.gov/medwatch.

FULL PRESCRIBING INFORMATION

1 INDICATIONS AND USAGE

FINACEA® (azelaic acid) Gel, 15% is indicated for topical treatment of the inflammatory papules and pustules of mild to moderate rosacea. Although some reduction of erythema which was present in patients with papules and pustules of rosacea occurred in clinical studies, efficacy for treatment of erythema in rosacea in the absence of papules and pustules has not been evaluated.

2 DOSAGE AND ADMINISTRATION

- Apply and gently massage a thin layer of FINACEA Gel into the affected areas on the face twice daily (morning and evening).
- Use only very mild soaps or soapless cleansing lotion before application of FINACEA Gel.
- Cosmetics may be applied after the application of FINACEA Gel has dried.
- Avoid the use of occlusive dressings or wrappings.
- Instruct patients to avoid spicy foods, thermally hot foods and drinks, alcoholic beverages.
- Patients should be reassessed if no improvement is observed upon completing 12 weeks of therapy.
- Not for oral, ophthalmic or intravaginal use.

3 DOSAGE FORMS AND STRENGTHS

FINACEA (azelaic acid) Gel, 15% is a white to yellowish white opaque gel. Each gram of FINACEA Gel contains 0.15 gm of azelaic acid (15% w/w).

4 CONTRAINDICATIONS

None.

5 WARNINGS AND PRECAUTIONS

5.1 Hypersensitivity

Hypersensitivity reactions, including cases of angioedema, eye swelling, facial swelling, dyspnea, urticaria, and adverse skin reactions, have been reported during post marketing surveillance.

Avoid the use of FINACEA Gel in patients with known hypersensitivity to any component of the gel. If hypersensitivity develops during treatment, discontinue FINACEA Gel and institute appropriate therapy.

5.2 Skin Reactions

Skin irritation (i.e. pruritus, burning or stinging) may occur during use of FINACEA Gel, usually during the first few weeks of treatment. If sensitivity or severe irritation develops and persists, discontinue treatment and institute appropriate therapy.

There have been isolated reports of hypopigmentation after use of azelaic acid. Since azelaic acid has not been well studied in patients with dark complexion, monitor these patients for early signs of hypopigmentation.

5.3 Eye and Mucous Membranes Irritation

Avoid contact with the eyes, mouth and other mucous membranes. If FINACEA Gel does come in contact with the eyes, wash the eyes with large amounts of water and consult a physician if eye irritation persists [see Adverse Reactions (6.2)].

5.4 Exacerbation of Asthma

Worsening of asthma has been reported in patients using azelaic acid formulations including FINACEA Gel. Consult a physician if asthma is exacerbated with use of FINACEA Gel.

6 ADVERSE REACTIONS

6.1 Clinical Trials Experience

Because clinical trials are conducted under widely varying conditions, adverse reaction rates observed in the clinical trials of a drug cannot be directly compared to rates in the clinical trials of another drug and may not reflect the rates observed in practice.

In two vehicle-controlled and one active-controlled U.S. clinical trials, treatment safety was monitored in 788 subjects who used twice-daily FINACEA Gel for 12 weeks (N=333) or 15 weeks (N=124), or the gel vehicle (N=331) for 12 weeks. In all three trials, the most common treatment-related adverse events were: burning/stinging/tingling (29%), pruritus (11%), scaling/dry skin/xerosis (8%) and erythema/irritation (4%). In the active-controlled trial, overall adverse reactions (including burning, stinging/tingling, dryness/tightness/scaling, itching, and erythema/irritation/redness) were 19.4% (24/124) for FINACEA Gel compared to 7.1% (9/127) for the active comparator gel at 15 weeks.

Table 1: Adverse Events Occurring in ≥1% of Subjects in the Rosacea Trials by Treatment Group and Maximum Intensity*
 | FINACEA Gel, 15%; N=457; (100%) |  |  | Vehicle; N=331; (100%)
 | Mild; N=99; (22%) | Moderate; N=61; (13%) | Severe; N=27; (6%) | Mild; N=46; (14%) | Moderate; N=30; (9%) | Severe; N=5; (2%)
Burning/stinging/tingling | 71 (16%) | 42 (9%) | 17 (4%) | 8 (2%) | 6 (2%) | 2 (1%)
Pruritus | 29 (6%) | 18 (4%) | 5 (1%) | 9 (3%) | 6 (2%) | 0 (0%)
Scaling/dry skin/xerosis | 21 (5%) | 10 (2%) | 5 (1%) | 31 (9%) | 14 (4%) | 1 (<1%)
Erythema/irritation | 6 (1%) | 7 (2%) | 2 (<1%) | 8 (2%) | 4 (1%) | 2 (1%)
Contact dermatitis | 2 (<1%) | 3 (1%) | 0 (0%) | 1 (<1%) | 0 (0%) | 0 (0%)
Edema | 3 (1%) | 2 (<1%) | 0 (0%) | 3 (1%) | 0 (0%) | 0 (0%)
Acne | 3 (1%) | 1 (<1%) | 0 (0%) | 1 (<1%) | 0 (0%) | 0 (0%)
*Subjects may have >1 cutaneous adverse event; thus, the sum of the frequencies of preferred terms may exceed the number of subjects with at least 1 cutaneous adverse event.

In patients using azelaic acid formulations, the following adverse events have been reported: worsening of asthma, vitiligo, depigmentation, small depigmented spots, hypertrichosis, reddening (signs of keratosis pilaris) and exacerbation of recurrent herpes labialis.

Local Tolerability Studies

FINACEA Gel and its vehicle caused irritant reactions at the application site in human dermal safety studies. FINACEA Gel caused significantly more irritation than its vehicle in a cumulative irritation study. Some improvement in irritation was demonstrated over the course of the clinical trials, but this improvement might be attributed to subject dropouts. No phototoxicity or photoallergenicity were reported in human dermal safety studies.

6.2 Post-Marketing Experience

The following adverse reactions have been identified post approval of FINACEA Gel. Because these reactions are reported voluntarily from a population of uncertain size, it is not always possible to reliably estimate the frequency or establish a causal relationship to drug exposure:

Eyes: iridocyclitis upon accidental exposure of the eyes to FINACEA Gel

Hypersensitivity: angioedema, eye swelling, facial swelling, urticaria.

Respiratory: worsening of asthma, dyspnea, wheezing,

7 DRUG INTERACTIONS

There have been no formal studies of the interaction of FINACEA Gel with other drugs.

8 USE IN SPECIFIC POPULATIONS

8.1 Pregnancy

Teratogenic Effects: Pregnancy Category B

There are no adequate and well-controlled studies in pregnant women. Therefore, FINACEA Gel should be used during pregnancy only if the potential benefit justifies the potential risk to the fetus.

Dermal embryofetal developmental toxicology studies have not been performed with azelaic acid, 15% gel. Oral embryofetal developmental studies were conducted with azelaic acid in rats, rabbits, and cynomolgus monkeys. Azelaic acid was administered during the period of organogenesis in all three animal species. Embryotoxicity was observed in rats, rabbits, and monkeys at oral doses of azelaic acid that generated some maternal toxicity. Embryotoxicity was observed in rats given 2500 mg/kg/day [162 times the maximum recommended human dose (MRHD) based on body surface area (BSA)], rabbits given 150 or 500 mg/kg/day (19 or 65 times the MRHD based on BSA) and cynomolgus monkeys given 500 mg/kg/day (65 times the MRHD based on BSA) azelaic acid. No teratogenic effects were observed in the oral embryofetal developmental studies conducted in rats, rabbits and cynomolgus monkeys.

An oral peri- and post-natal developmental study was conducted in rats. Azelaic acid was administered from gestational day 15 through day 21 postpartum up to a dose level of 2500 mg/kg/day. Embryotoxicity was observed in rats at an oral dose of 2500 mg/kg/day (162 times the MRHD based on BSA) that generated some maternal toxicity. In addition, slight disturbances in the post-natal development of fetuses was noted in rats at oral doses that generated some maternal toxicity (500 and 2500 mg/kg/day; 32 and 162 times the MRHD based on BSA). No effects on sexual maturation of the fetuses were noted in this study.

8.3 Nursing Mothers

It is not known whether azelaic acid is excreted in human milk; however, in vitro studies using equilibrium dialysis were conducted to assess the potential for human milk partitioning. The studies demonstrated that, at an azelaic acid concentration of 25 µg/mL, the milk/plasma distribution coefficient was 0.7 and the milk/buffer distribution was 1.0. These data indicate that passage of drug into maternal milk may occur. Since less than 4% of a topically applied dose of 20% azelaic acid cream is systemically absorbed, the uptake of azelaic acid into maternal milk is not expected to cause a significant change from baseline azelaic acid levels in the milk. Nevertheless, a decision should be made to discontinue nursing or to discontinue the drug, taking into account the importance of the drug to the mother.

8.4 Pediatric Use

Safety and effectiveness of FINACEA Gel in pediatric patients have not been established.

8.5 Geriatric Use

Clinical studies of FINACEA Gel did not include sufficient numbers of subjects aged 65 and over to determine whether they respond differently from younger subjects.

11 DESCRIPTION

FINACEA (azelaic acid) Gel, 15%, is an aqueous gel which contains azelaic acid, a naturally-occurring saturated dicarboxylic acid. Chemically, azelaic acid is 1,7-heptanedicarboxylic acid. The molecular formula for azelaic acid is C9 H16 O4. It has the following structure:

Azelaic acid has a molecular weight of 188.22. It is a white, odorless crystalline solid. It is poorly soluble in water at 20°C (0.24%) but freely soluble in boiling water and in ethanol.

FINACEA Gel is a white to yellowish white opaque gel for topical use; each gram contains 0.15 gm azelaic acid (15%w/w) in an aqueous gel base containing benzoic acid (as a preservative), disodium EDTA, lecithin, medium-chain triglycerides, polyacrylic acid, polysorbate 80, propylene glycol, purified water, and sodium hydroxide to adjust pH.

12 CLINICAL PHARMACOLOGY

12.1 Mechanism of Action

The mechanism(s) by which azelaic acid interferes with the pathogenic events in rosacea are unknown.

12.2 Pharmacodynamics

The pharmacodynamics of azelaic acid in association with the treatment of rosacea is unknown.

12.3 Pharmacokinetics

The percutaneous absorption of azelaic acid after topical application of FINACEA Gel could not be reliably determined. Mean plasma azelaic acid concentrations in rosacea subjects treated with FINACEA Gel twice daily for at least 8 weeks are in the range of 42 to 63.1 ng/mL. These values are within the maximum concentration range of 24.0 to 90.5 ng/mL observed in rosacea subjects treated with vehicle only. This indicates that FINACEA Gel does not increase plasma azelaic acid concentration beyond the range derived from nutrition and endogenous metabolism.

In vitro and human data suggest negligible cutaneous metabolism of ^3H-azelaic acid after topical application of 20% azelaic acid cream. Azelaic acid is mainly excreted unchanged in the urine, but undergoes some ß oxidation to shorter chain dicarboxylic acids.

13 NONCLINICAL TOXICOLOGY

13.1 Carcinogenesis, Mutagenesis, Impairment of Fertility

Systemic long-term animal studies have not been performed to evaluate the carcinogenic potential of azelaic acid. In a 26-week dermal carcinogenicity study using transgenic (Tg.AC) mice, FINACEA Gel and the gel vehicle, when applied once or twice daily, did not increase the number of female Tg.AC animals with papillomas at the treatment site. No statistically significant increase in the number of animals with papillomas at the treatment site was observed in male Tg.AC animals after once daily application. After twice daily application, FINACEA Gel and the gel vehicle induced a statistically significant increase in the number of male animals with papillomas at the treatment site when compared to untreated males. This suggests that the positive effect may be associated with the vehicle application. The clinical relevance of the findings in animals to humans is not clear.

Azelaic acid was not mutagenic or clastogenic in a battery of in vitro [Ames assay, HGPRT in V79 cells (Chinese hamster lung cells), and chromosomal aberration assay in human lymphocytes] and in vivo (dominant lethal assay in mice and mouse micronucleus assay) genotoxicity tests.

Oral administration of azelaic acid at dose levels up to 2500 mg/kg/day (162 times the MRHD based on BSA) did not affect fertility or reproductive performance in male or female rats.

14 CLINICAL STUDIES

FINACEA Gel was evaluated for the treatment of mild to moderate papulopustular rosacea in two multicenter, randomized, double-blind, vehicle-controlled, 12-week clinical trials having identical protocols and involving a total of 664 (active: 333; vehicle: 331) subjects aged 21 to 86 years (mean age = 49). Overall, 92.5% of subjects were Caucasian and 73% of subjects were female. Enrolled subjects had mild to moderate rosacea with a mean lesion count of 18 (range 8 to 60) inflammatory papules and pustules. The following subjects were excluded: a) those without papules and pustules; b) those with nodules, rhinophyma, or ocular involvement and c) those with a history of hypersensitivity to propylene glycol or to any other ingredients of the study drug. FINACEA Gel or its vehicle were to be applied twice daily for 12 weeks; no other topical or systemic medication affecting the course of rosacea and/or evaluability was to be used during the studies. Subjects were instructed to avoid spicy foods, thermally hot food/drink and alcoholic beverages during the study. Subjects were also instructed to use only very mild soaps or soapless cleansing lotion for facial cleansing.

The primary efficacy endpoints included both 1) change from baseline in inflammatory lesion counts as well as 2) success defined as a score of “clear” or “minimal” with at least a 2-step reduction from baseline on the Investigator’s Global Assessment (IGA), defined as follows below:

CLEAR:

No papules and/or pustules; no or residual erythema; no or mild to moderate telangiectasia

MINIMAL:

Rare papules and/or pustules; residual to mild erythema; mild to moderate telangiectasia

MILD:

Few papules and/or pustules; mild erythema; mild to moderate telangiectasia

MILD TO MODERATE:

Distinct number of papules and/or pustules; mild to moderate erythema; mild to moderate telangiectasia

MODERATE:

Pronounced number of papules and/or pustules; moderate erythema; mild to moderate telangiectasia

MODERATE TO SEVERE:

Many papules and/or pustules, occasionally with large inflamed lesions; moderate erythema; moderate degree of telangiectasia

SEVERE:

Numerous papules and/or pustules, occasionally with confluent areas of inflamed lesions; moderate or severe erythema; moderate or severe telangiectasia

Primary efficacy assessment was based on the “intent-to-treat” (ITT) population with the “last observation carried forward” (LOCF).

Both trials demonstrated a statistically significant difference in favor of FINACEA Gel over its vehicle in both reducing the number of inflammatory papules and pustules associated with rosacea (Table 2) as well as demonstrating success on the IGA in the ITT-LOCF population at the end of treatment.

Table 2: Inflammatory Papules and Pustules (ITT population)*
 | Study One; FINACEA Gel, 15%; N=164 | Study One; VEHICLE; N=165 | Study Two; FINACEA Gel, 15%; N=167 | Study Two; VEHICLE; N=166
Mean Lesion Count; Baseline | 17.5 | 17.6 | 17.9 | 18.5
End of Treatment* | 6.8 | 10.5 | 9.0 | 12.1
Mean Percent Reduction End of Treatment* | 57.9% | 39.9% | 50.0% | 38.2%
*ITT population with last observation carried forward (LOCF)

Although some reduction of erythema which was present in subjects with papules and pustules of rosacea occurred in clinical trials, efficacy for treatment of erythema in rosacea in the absence of papules and pustules has not been evaluated.

FINACEA Gel was superior to the vehicle with regard to success based on the IGA of rosacea on a 7-point static score at the end of treatment (ITT population; Table 3).

Table 3: Investigator’s Global Assessment at the End of Treatment*
 | Study One; FINACEA Gel, 15%; N=164 | Study One; VEHICLE; N=165 | Study Two; FINACEA Gel, 15%; N=167 | Study Two; VEHICLE; N=166
Clear, Minimal or Mild at End of Treatment; (% of Subjects) | 61% | 40% | 61% | 48%
*ITT population with last observation carried forward (LOCF)

16 HOW SUPPLIED/STORAGE AND HANDLING

Product: 50090-3032

NDC: 50090-3032-0 50 g in a TUBE / 1 in a CARTON

17 PATIENT COUNSELING INFORMATION

Inform patients using FINACEA Gel of the following information and instructions:

- For external use only.
- Before applying FINACEA Gel, cleanse affected area(s) with a very mild soap or a soapless cleansing lotion and pat dry with a soft towel.
- Avoid use of alcoholic cleansers, tinctures and astringents, abrasives and peeling agents.
- Avoid contact with the eyes, mouth and other mucous membranes. If FINACEA Gel does come in contact with the eyes, wash the eyes with large amounts of water and consult your physician if eye irritation persists.
- Wash hands immediately following application of FINACEA Gel.
- Cosmetics may be applied after the application of FINACEA Gel has dried.
- Avoid the use of occlusive dressings or wrappings.
- Skin irritation (e.g., pruritus, burning, or stinging) may occur during use of FINACEA Gel, usually during the first few weeks of treatment. If irritation is excessive or persists, or allergic reactions occur, discontinue use and consult your physician.
- If allergic reactions occur, discontinue use and consult their healthcare providers.
- Advise patients to report any worsening of asthma to their healthcare providers.
- Report abnormal changes in skin color to their healthcare providers.
- To help manage rosacea, avoid any triggers that may provoke erythema, flushing, and blushing. These triggers can include spicy and thermally hot food and drinks such as hot coffee, tea, or alcoholic beverages.
- FINACEA Gel comes in a tube and a pump:
  - Tube instructions: Remove the cap before use. Squeeze the tube to dispense a small amount of FINACEA Gel.
  - Pump instructions:
    - Remove the cap before use. Depress the pump to dispense a small amount of FINACEA Gel. At first use, the pump may have to be depressed repeatedly until product is dispensed.
    - Discard the pump 8 weeks after opening.

© 2002, Bayer HealthCare Pharmaceuticals Inc. All rights reserved.

Manufactured for:

Bayer HealthCare Pharmaceuticals Inc.

Whippany, NJ 07981

Manufactured in Italy